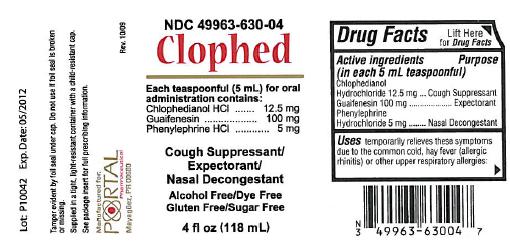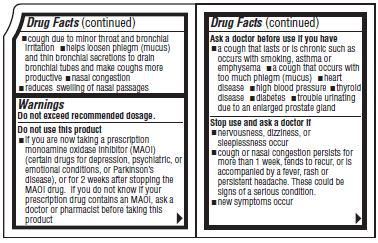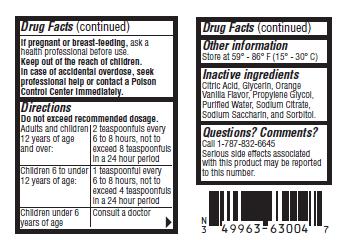 DRUG LABEL: Clophed
NDC: 49963-630 | Form: LIQUID
Manufacturer: Portal Pharmaceutical
Category: otc | Type: HUMAN OTC DRUG LABEL
Date: 20101230

ACTIVE INGREDIENTS: Chlophedianol Hydrochloride 12.5 mg/5 mL; Guaifenesin 100 mg/5 mL; Phenylephrine Hydrochloride 5 mg/5 mL
INACTIVE INGREDIENTS: Citric Acid; Glycerin; Propylene Glycol; Water; Sodium Citrate; Saccharin Sodium; Sorbitol

Chlophed

Drug Facts

Active ingredients
(in each 5 mL teaspoonful)
Chlophedianol Hydrochloride 12.5 mg
Guaifenesin 100 mg
Phenylephrine Hydrochloride 5 mg

PURPOSE

Cough Suppressant
Expectorant
Nasal Decongestant

Uses

temporarily relieves these symptoms due to the common cold, hay fever (allergic rhinitis) or other upper respiratory allergies:

- cough due to minor throat and bronchial irritation
- helps loosen phelgm (mucus) and thin bronchial secretions to drain bronchial tubes and make coughs more productive
- nasal congestion
- reduces swelling of the nasal passages

Warnings

Do not exceed recommended dosage.

Do not use this product

- if you are now taking a prescription monoamine oxidase inhibitor (MAOI) (certain drugs for depression, psychiatric, or emotional conditions, or Parkinson's disease), or for 2 weeks after stopping the MAOI drug. If you do not know if your prescription drug contains an MAOI, ask a doctor or pharmacist before taking this product

Ask a doctor before use if you have

- a cough that lasts or is chronic such as occurs with smoking, asthma or emphysema
- a cough that occurs with too much phlegm (mucus)
- heart disease
- high blood pressure
- thyroid disease
- diabetes
- trouble urinating due to an enlarged prostate gland

Stop use and ask a doctor if

- nervousness, dizziness, or sleeplessness occur
- cough or nasal congestion persists for more than 1 week, tends to recur, or is accompanied by a fever, rash or persistent headache. These could be signs of a serious condition.
- new symptoms occur

If pregnant or breast-feeding,

ask a health professional before use.

Keep out of the reach of children.

In case of accidental overdose, seek professional help or contact a Poison Control Center immediately.

Directions

Do not exceed recommended dosage.

Adults and children 12 years of age and over: | 2 teaspoonfuls every 6 to 8 hours, not to exceed 8 teaspoonfuls in a 24 hour period
Children 6 to under 12 years of age: | 1 teaspoonful every 6 to 8 hours, not to exceed 4 teaspoonfuls in a 24 hour period
Children under 6 years of age | Consult a doctor

Other information

Store at 59° - 86° F(15° - 30° C)

Inactive ingredients

Citric Acid, Glycerin, Orange Vanilla Flavor, propylene Glycol, Purified Water, Sodium Citrate, Sodium Saccharin, and Sorbitol.

Questions? Comments?

Call 1-787-832-6645
Serious side effects associated with this product may be reported to this number.

Product Packaging:

Packaging below represents the labeling currently used:
Principal display panel and side panel for 118 mL label:
NDC 49963-630-04
Clophed
Each teaspoonful (5 mL) for oral administration contains:
Chlophedianol HCl.....................................12.5 mg
Guaifenesin...............................................100 mg
Phenylephrine HCl.........................................5 mg
Cough Suppressant/Expectorant/Nasal Decongestant
Alcohol Free/Dye Free/Gluten Free/Sugar Free
4 fl oz (118 mL)
Tamper evident by foil seal under cap. Do not use if foil seal is broken or missing.
Supplied in a tight, light-resistant container with a child-resistant cap.
See package insert for full prescribing information.
Manufactured for:
Portal Pharmaceutical
Mayaguez, PR 00680 Rev. 10/09